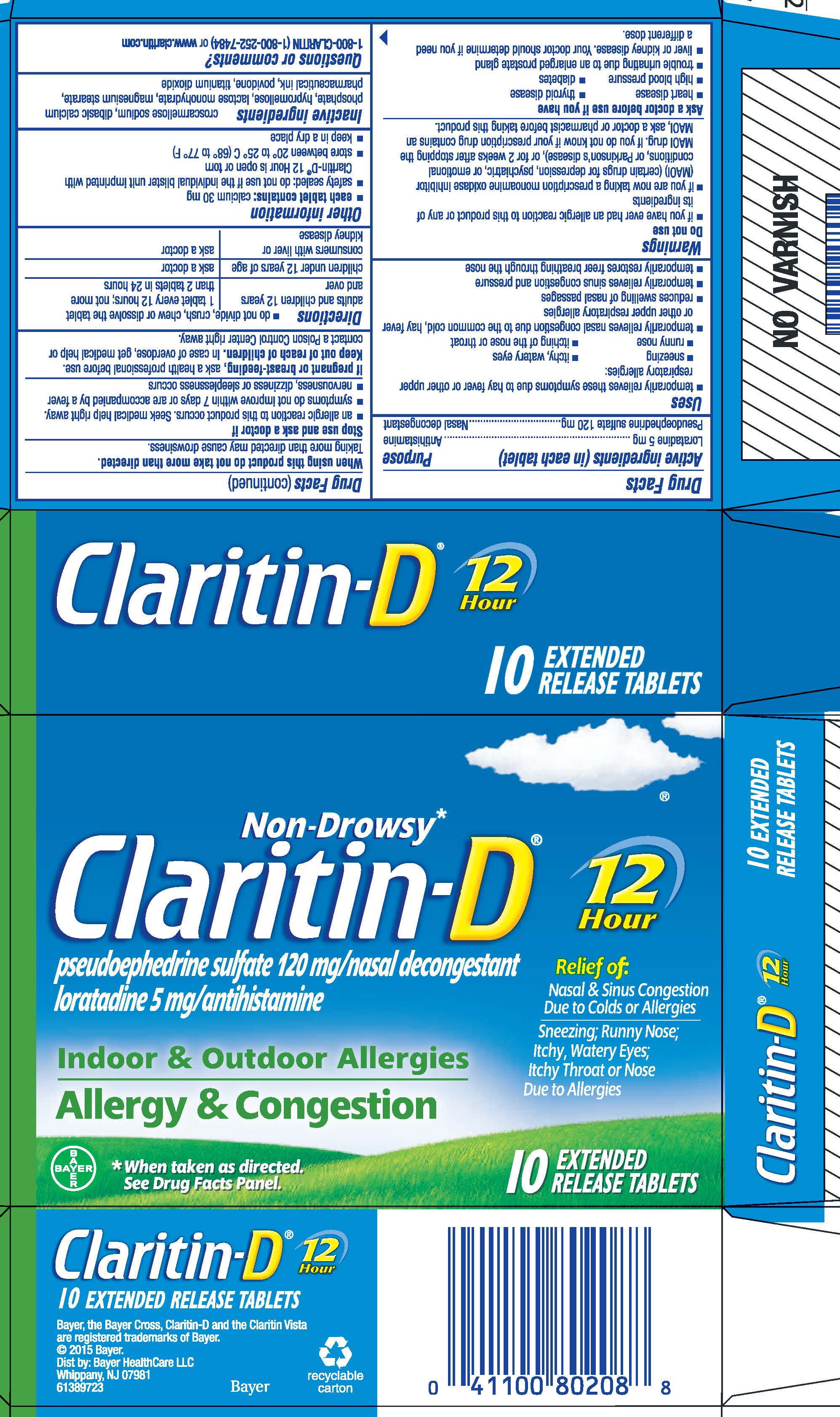 DRUG LABEL: Claritin-D
NDC: 11523-7162 | Form: TABLET, EXTENDED RELEASE
Manufacturer: Bayer HealthCare LLC.
Category: otc | Type: HUMAN OTC DRUG LABEL
Date: 20251205

ACTIVE INGREDIENTS: LORATADINE 5 mg/1 1; PSEUDOEPHEDRINE SULFATE 120 mg/1 1
INACTIVE INGREDIENTS: CROSCARMELLOSE SODIUM; CALCIUM PHOSPHATE, DIBASIC, ANHYDROUS; HYPROMELLOSES; LACTOSE MONOHYDRATE; MAGNESIUM STEARATE; POVIDONE; TITANIUM DIOXIDE

Claritin-D®
12 Hour

Drug Facts

ACTIVE INGREDIENT

Active ingredient (in each tablet) | Purpose
Loratadine 5 mg | Antihistamine
Pseudoephedrine sulfate 120 mg | Nasal decongestant

Uses

- temporarily relieves these symptoms due to hay fever or other upper respiratory allergies:
  - sneezing
  - itchy, watery eyes
  - runny nose
  - itching of the nose or throat
- temporarily relieves nasal congestion due to the common cold, hay fever or other upper respiratory allergies
- reduces swelling of nasal passages
- temporarily relieves sinus congestion and pressure
- temporarily restores freer breathing through the nose

Warnings

Do not use

- if you have ever had an allergic reaction to this product or any of its ingredients
- if you are now taking a prescription monoamine oxidase inhibitor (MAOI) (certain drugs for depression, psychiatric, or emotional conditions, or Parkinson's disease), or for 2 weeks after stopping the MAOI drug. If you do not know if your prescription drug contains an MAOI, ask a doctor or pharmacist before taking this product.

Ask a doctor before use if you have

- heart disease
- thyroid disease
- high blood pressure
- diabetes
- trouble urinating due to an enlarged prostate gland
- liver or kidney disease. Your doctor should determine if you need a different dose.

When using this product do not take more than directed.

Taking more than directed may cause drowsiness.

Stop use and ask a doctor if

- an allergic reaction to this product occurs. Seek medical help right away.
- symptoms do not improve within 7 days or are accompanied by a fever
- nervousness, dizziness or sleeplessness occurs

PREGNANCY OR BREAST FEEDING

If pregnant or breast-feeding, ask a health professional before use.

Keep out of reach of children. In case of overdose, get medical help or contact a Poison Control Center right away.

Directions

- do not divide, crush, chew or dissolve the tablet

adults and children 12 years and over | 1 tablet every 12 hours; not more than 2 tablets in 24 hours
children under 12 years of age | ask a doctor
consumers with liver or kidney disease | ask a doctor

Other information

- each tablet contains: calcium 30 mg
- safety sealed: do not use if the individual blister unit imprinted with Claritin-D® 12 Hour is open or torn
- store between 20° to 25°C (68° to 77°F)
- keep in a dry place

Inactive ingredients

croscarmellose sodium, dibasic calcium phosphate, hypromellose, lactose monohydrate, magnesium sterarate, pharmaceutical ink, povidone, titanium dioxide

Questions or comments?

1-800-CLARITIN (1-800-252-7484) or www.claritin.com

PRINCIPAL DISPLAY PANEL - Carton

NDC 11523-7162-1

Non-Drowsy*
Claritin-D®
pseudoephedrine sulfate 120 mg/nasal decongestant
loratadine 5 mg/antihistamine

Indoor & Outdoor Allergies
Allergy & Congestion

12
Hour

Relief of:
Nasal & Sinus Congestion
Due to Colds or Allergies
Sneezing; Runny Nose;
Itchy, Watery Eyes;
Itchy Throat or Nose
Due to Allergies

* When taken as directed. See Drug Facts Panel.

10
EXTENDED
RELEASE TABLETS